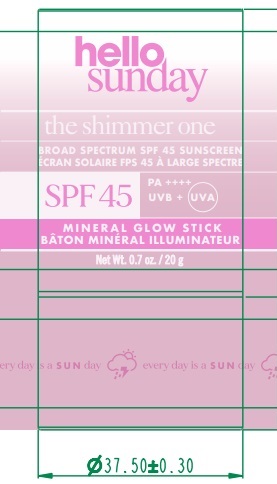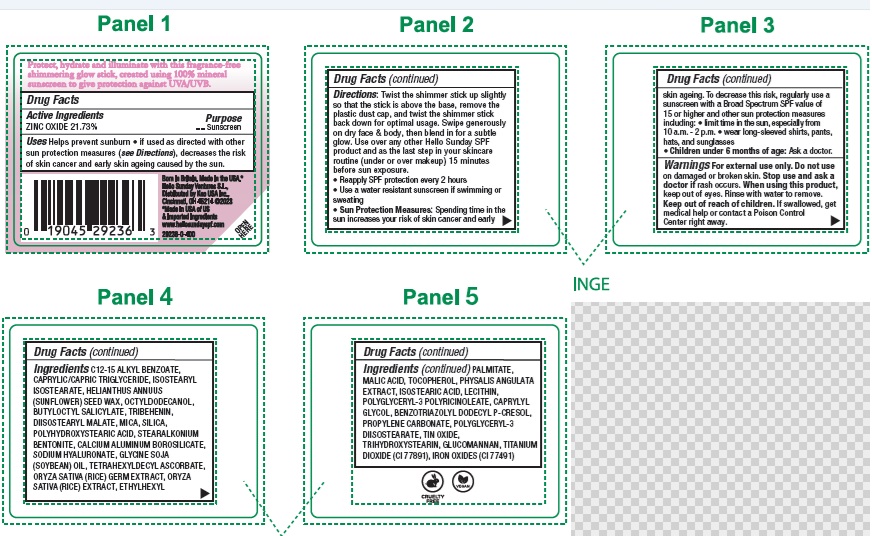 DRUG LABEL: Hello Sunday The Shimmer One Mineral Glow SPF 45
NDC: 10596-805 | Form: STICK
Manufacturer: Kao USA Inc.
Category: otc | Type: HUMAN OTC DRUG LABEL
Date: 20250131

ACTIVE INGREDIENTS: ZINC OXIDE 217.3 mg/1 g
INACTIVE INGREDIENTS: ISOSTEARYL ISOSTEARATE; HYALURONATE SODIUM; RICE GERM; HELIANTHUS ANNUUS SEED WAX; TRIHYDROXYSTEARIN; TETRAHEXYLDECYL ASCORBATE; OCTYLDODECANOL; BUTYLOCTYL SALICYLATE; TRIBEHENIN; DIISOSTEARYL MALATE; TOCOPHEROL; MICA; ALKYL (C12-15) BENZOATE; SILICON DIOXIDE; POLYHYDROXYSTEARIC ACID (2300 MW); CALCIUM ALUMINUM BOROSILICATE; ETHYLHEXYL PALMITATE; MALIC ACID; KONJAC MANNAN; PHYSALIS ANGULATA WHOLE; CAPRYLYL GLYCOL; ISOSTEARIC ACID; POLYGLYCERYL-3 DIISOSTEARATE; LECITHIN, SOYBEAN; MEDIUM-CHAIN TRIGLYCERIDES; SOYBEAN OIL; STANNOUS OXIDE; POLYGLYCERYL-3 PENTARICINOLEATE; TITANIUM DIOXIDE; FERRIC OXIDE RED; BENZOTRIAZOLYL DODECYL P-CRESOL; PROPYLENE CARBONATE

Hello Sunday The Shimmer One Mineral Glow SPF 45

Active Ingredients

ZINC OXIDE 21.73%

Purpose

Sunscreen

Uses

- helps prevent sunburn
- if used as directed with other sun protection measures (see Directions), decreases the risk of skin cancer and early skin ageing caused by the sun.

Directions

- Twist the shimmer stick up slightly so that the stick is above the base, remove the plastic dust cap, and twist the shimmer stick back down for optimal usage. Swipe generously on dry face & body, then blend in for a subtle glow. Use over any other Hello Sunday SPF

product and as the last step in your skincare routine (under or over makeup) 15 minutes before sun exposure.

- Reapply SPF protection every 2 hours
- Use a water resistant sunscreen if swimming or sweating
- Sun Protection Measures: Spending time in the sun increases your risk of skin cancer and early skin ageing. To decrease this risk, regularly use a sunscreen with a Broad Spectrum SPF value of 15 or higher and other sun protection measures including:
- limit time in the sun, especially from 10 a.m. – 2 p.m.
- wear long-sleeved shirts, pants, hats, and sunglasses
- Children under 6 months of age: Ask a doctor.

Warnings

For external use only

Do not use

on damaged or broken skin

Stop use and ask a doctor if

rash occurs

When using this product

keep out of eyes. Rinse with water to remove.

Keep out of reach of children.

If swallowed, get medical help or contact a Poison Control Center right away.

Ingredients

C12-15 ALKYL BENZOATE, CAPRYLIC/CAPRIC TRIGLYCERIDE, ISOSTEARYL ISOSTEARATE, HELIANTHUS ANNUUS (SUNFLOWER) SEED WAX, OCTYLDODECANOL, BUTYLOCTYL SALICYLATE, TRIBEHENIN, DIISOSTEARYL MALATE, MICA, SILICA, POLYHYDROXYSTEARIC ACID, STEARALKONIUM BENTONITE, CALCIUM ALUMINUM BOROSILICATE, SODIUM HYALURONATE, GLYCINE SOJA (SOYBEAN) OIL, TETRAHEXYLDECYL ASCORBATE, ORYZA SATIVA (RICE) GERM EXTRACT, ORYZA SATIVA (RICE) EXTRACT, ETHYLHEXYL PALMITATE, MALIC ACID, TOCOPHEROL, PHYSALIS ANGULATA EXTRACT, ISOSTEARIC ACID, LECITHIN, POLYGLYCERYL-3 POLYRICINOLEATE, CAPRYLYL GLYCOL, BENZOTRIAZOLYL DODECYL P-CRESOL, PROPYLENE CARBONATE, POLYGLYCERYL-3 DIISOSTEARATE, TIN OXIDE, TRIHYDROXYSTEARIN, GLUCOMANNAN, TITANIUM DIOXIDE (CI 77891), IRON OXIDES (CI 77491)